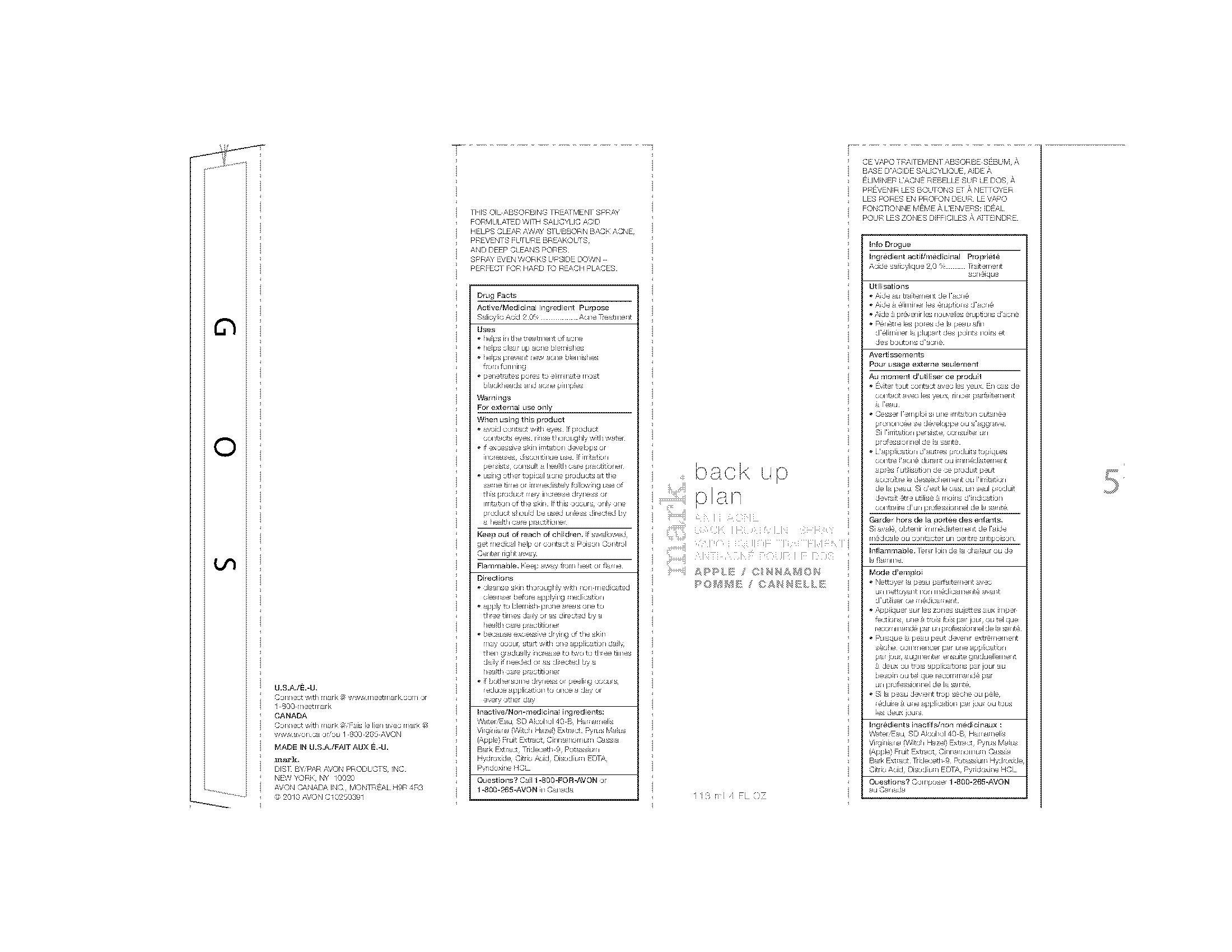 DRUG LABEL: mark. back up plan
NDC: 10096-0192 | Form: SPRAY
Manufacturer: Avon Products, Inc.
Category: otc | Type: HUMAN OTC DRUG LABEL
Date: 20091229

ACTIVE INGREDIENTS: Salicylic Acid 4.72 mL/118 mL
INACTIVE INGREDIENTS: WATER; POTASSIUM HYDROXIDE

Drug Facts

Active/Medicinal ingredient Purpose

Salicylic Acid 2.0%..................Acne Treatment

Uses
• helps in the treatment of acne
• helps clear up acne blemishes
• helps prevent new acne blemishes
from forming
• penetrates pores to eliminate most
blackheads and acne pimples

Warnings
For external use only

When using this product
• avoid contact with eyes. If product
contacts eyes, rinse thoroughly with water.
• if excessive skin irritation develops or
increases, discontinue use. If irritation
persists, consult a health care practitioner.
• using other topical acne products at the
same time or immediately following use of
this product may increase dryness or
irritation of the skin. If this occurs, only one
product should be used unless directed by
a health care practitioner

Keep out of reach of children. If swallowed,
get medical help or contact a Poison Control
Center right away.

STORAGE AND HANDLING

Flammable. Keep away from heat or flame.

Directions
• cleanse skin thoroughly with non-medicated
cleanser before applying medication
• apply to blemish-prone areas one to
three times daily or as directed by a
health care practitioner
• because excessive drying of the skin
may occur, start with one application daily,
then gradually increase to two to three times
daily if needed or as directed by a
health care practitioner
• if bothersome dryness or peeling occurs,
reduce application to once a day or
every other day

Inactive/Non-medicinal ingredients:
Water/Eau, SD Alcohol 40-B, Hamamelis
Virginiana (Witch Hazel) Extract, Pyrus Malus
(Apple) Fruit Extract, Cinnamomum Cassia
Bark Extract, Trideceth-9, Potassium
Hydroxide, Citric Acid, Disodium EDTA,
Pyridoxine HCL.

Questions? Call 1-800-FOR-AVON or
1-800-265-AVON in Canada